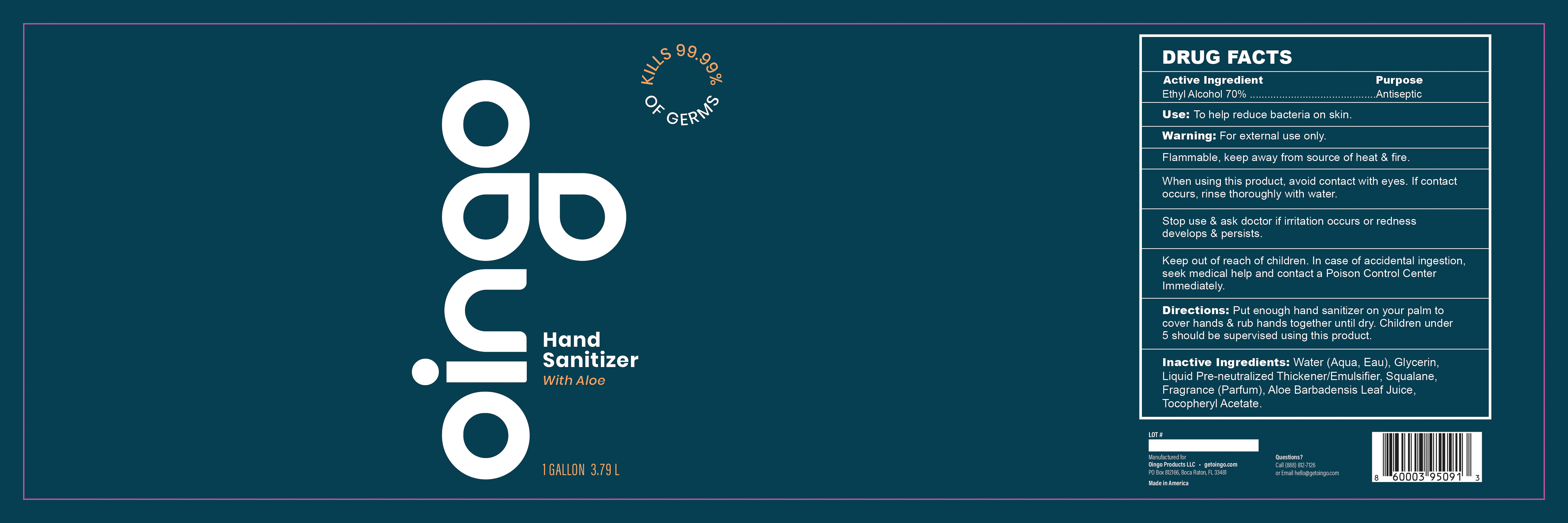 DRUG LABEL: Hand Sanitizer with Aloe
NDC: 79436-100 | Form: GEL
Manufacturer: Oingo Products LLC
Category: otc | Type: HUMAN OTC DRUG LABEL
Date: 20200728

ACTIVE INGREDIENTS: ALCOHOL 70 mL/100 mL
INACTIVE INGREDIENTS: WATER; .ALPHA.-TOCOPHEROL ACETATE, D-; SQUALANE; RAPIDGEL EZ1; ALOE VERA LEAF; GLYCERIN 1.45 mL/100 mL

Oingo Hand Sanitizer

Active Ingredient(s)

Alcohol 70% Purpose: Antiseptic

Purpose

Antiseptic, Hand Sanitizer

Use

To help reduce bacteria on skin.

Warnings

For external use only. Flammable. Keep away from heat & fire.

When using this product, avoid contact with eyes. If contact occurs, rinse thoroughly with water.

Stop use and ask a doctor if irritation occurs or redness develops & persists.

Keep out of reach of children. In case of accidental ingestion, seek medical help and contact a Poison Control Center Immediately.

Directions

Put enough hand sanitizer on your palm to cover hands & rub hands together until dry. Children 5 should be supervised using this product.

Inactive ingredients

Water (Aqua, Eau), Glycerin, Liquid Pre-neutralized Thickener/Emulsifier, Squalane, Fragrance (Parfum), Aloe Barbadensis Leaf Juice, Tocopheryl Acetate.

Recent Major Changes Section

Section 3:

To help reduce bacteria on skin. (07/2020)

Section 8:

Put enough hand sanitizer on your palm to cover hands & rub hands together until dry. Children 5 should be supervised using this product. (07/2020)

Package Label - Principal Display Panel

3.79 L NDC: 79436-100-01